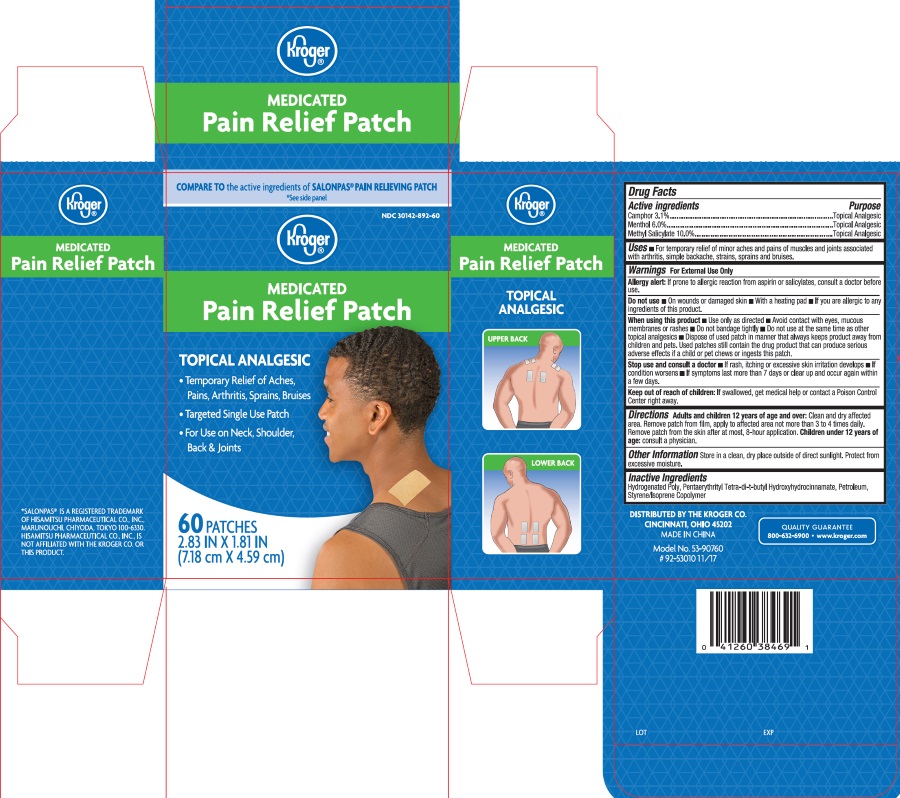 DRUG LABEL: Medicated Pain Relief Patch
NDC: 30142-892 | Form: PATCH
Manufacturer: Kroger Company
Category: otc | Type: HUMAN OTC DRUG LABEL
Date: 20251230

ACTIVE INGREDIENTS: CAMPHOR (SYNTHETIC) 3.1 g/100 g; MENTHOL 6 g/100 g; METHYL SALICYLATE 10 g/100 g
INACTIVE INGREDIENTS: HYDROGENATED POLYDECENE (550 MW); PENTAERYTHRITOL TETRAKIS(3-(3,5-DI-TERT-BUTYL-4-HYDROXYPHENYL)PROPIONATE); LIQUID PETROLEUM; STYRENE/ACRYLAMIDE COPOLYMER (MW 500000)

Medicated Pain Relief Patch

Active Ingredients

Active Ingredients Purpose

Camphor 3.1% ......................Topical Analgesic

Menthol 6.0% .......................Topical Analgesic

Methyl Salicylate 10.0% .......Topical Analgesic

For External Use Only

Allergy alert: If prone to allergic reaction from asprin or salicylates, consult a doctor before use

Do not use:

- On wounds or damaged skin
- With a heating pad
- If you are allergic to any ingredients of this product

When using this product

- Use only as directed
- Avoid contact with eyes, mucous membranes or rashes
- Do not bandage tighly
- Do not use at the same time as other topical analgesics
- Dispose of used patch in manner that keeps product away from childrens and pets. Used patches still contain the drug product that can produce serious adverse effects if a child or pet chews or ingests this patch.

Stop use and consult a doctor

- If rash, itching or excessive skin irritation develops
- If condition worsens
- if symptoms last more than 7 days or clear up and occur again with a few days

Keep out of reach of children

If swallowed, get medical help or contact a Poison Control Center right away

Uses

For temporary relief of minor aches and pains of muscles and joints associated with arthritis, simple backache, strains, sprains, and bruises.

Directions

Adults and children 12 years of age and over: Clean and dry affected area. Remove patch from film, apply to affected area not more than 3 to 4 times daily. Remove patch from the skin after at most, 8-hour application.

Children under 12 years of age: consult physician.

Inactive Ingredients

Hydrogenated Poly, Pentaerythrityl Tetra-di-t-butyl Hydroxyhydrocinnamate, Petroleum, Styrene / Isoprene Copolymer

Indication and Usage

For temporary relief of minor aches and pains.

OTHER SAFETY INFORMATION

DIST. BY
The Kroger Co.
Cincinnati, OH 45202

Made in China

Medicated Pain Relief Patch Label

Other Information: Store in clean, dy place outside of direct sunlight. Protect from excessive moisture.